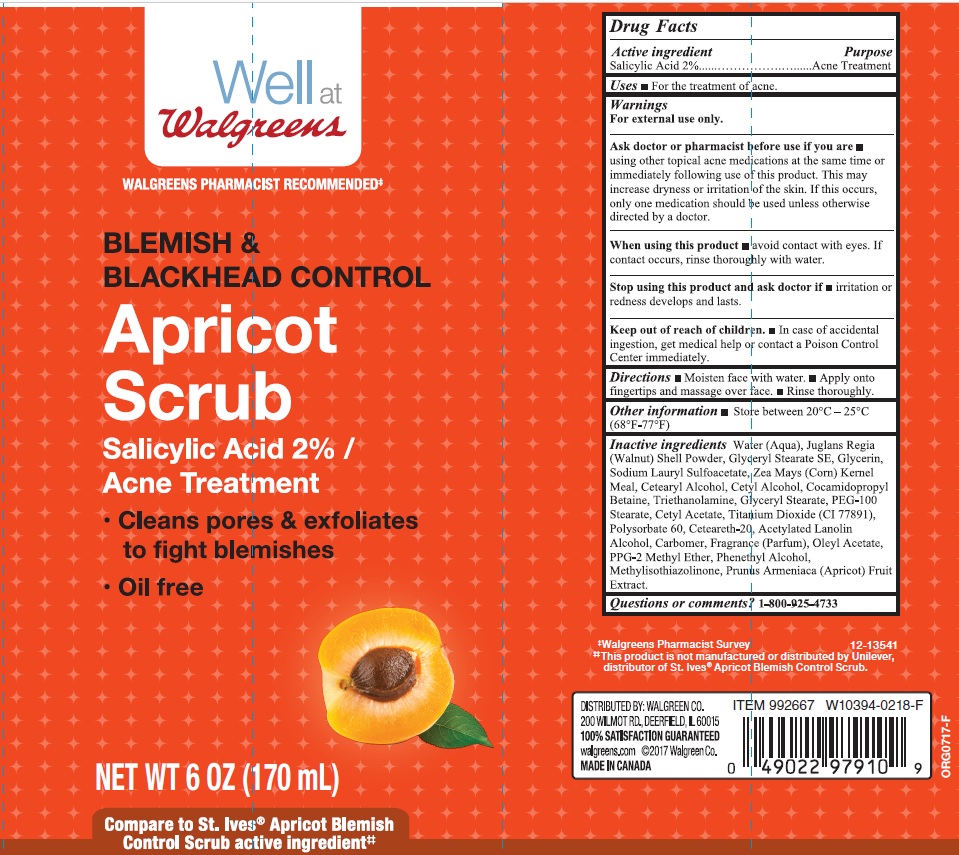 DRUG LABEL: Well at Walgreens Blemish and Blackhead Control Apricot
NDC: 0363-0830 | Form: LIQUID
Manufacturer: Walgreen Company
Category: otc | Type: HUMAN OTC DRUG LABEL
Date: 20180418

ACTIVE INGREDIENTS: SALICYLIC ACID 0.02 g/1 g
INACTIVE INGREDIENTS: WATER; JUGLANS REGIA SHELL; GLYCERYL STEARATE SE; GLYCERIN; SODIUM LAURYL SULFOACETATE; CORN GRAIN; CETOSTEARYL ALCOHOL; CETYL ALCOHOL; COCAMIDOPROPYL BETAINE; TROLAMINE; GLYCERYL MONOSTEARATE; PEG-100 STEARATE; CETYL ACETATE; TITANIUM DIOXIDE; POLYSORBATE 60; POLYOXYL 20 CETOSTEARYL ETHER; ACETYLATED LANOLIN ALCOHOLS; CARBOMER 934; 9-OCTADECENYL ACETATE, (9Z)-; PPG-2 METHYL ETHER; PHENYLETHYL ALCOHOL; METHYLISOTHIAZOLINONE; APRICOT

Drug Facts

Active ingredient

Salicylic Acid 2%

Purpose

Acne Treatment

Uses

- For the treatment of acne.

Warnings

For external use only.

Ask doctor or pharmacist before use if you are

- using other topical acne medications at the same time or immediately following use of this product. This may increase dryness or irritation of the skin. If this occurs, only one medication should be used unless otherwise directed by a doctor.

When using this product

- avoid contact with eyes. If contact occurs, rinse thoroughly with water.

Stop using this product and ask doctor if

- irritation or redness develops and lasts.

Keep out of reach of children.

- In case of accidental ingestion, get medical help or contact a Poison Control Center immediately.

Directions

- Moisten face with water.
- Apply onto fingertips and massage over face.
- Rinse thoroughly.

Other information

- store between 20°C - 25°C (68°F - 77°F)

Inactive ingredients

Water (Aqua), Glyceryl Stearate SE, Sodium Lauryl Sulfoacetate, Glycerin, Juglans Regia (Walnut) Shell Powder, Cetearyl Alcohol, Fragrance (Parfum), Cetyl Alcohol, Zea Mays (Corn) Kernel Meal, Triethanolamine, Cocamidoproypl Betaine, Glyceryl Stearate, PEG-100 Stearate, Cetyl Acetate, Titanium Dioxide (CI 77891), Polysorbate 60, Ceteareth-20, Acetylated Lanolin Alcohol, Carbomer, Oleyl Acetate, PPG-2 Methyl Ether, Phenethyl Alcohol, Methylisothiazolinone, Prunus Armeniaca (Apricot) Fruit Extract.

Questions or comments?

1-800-925-4733